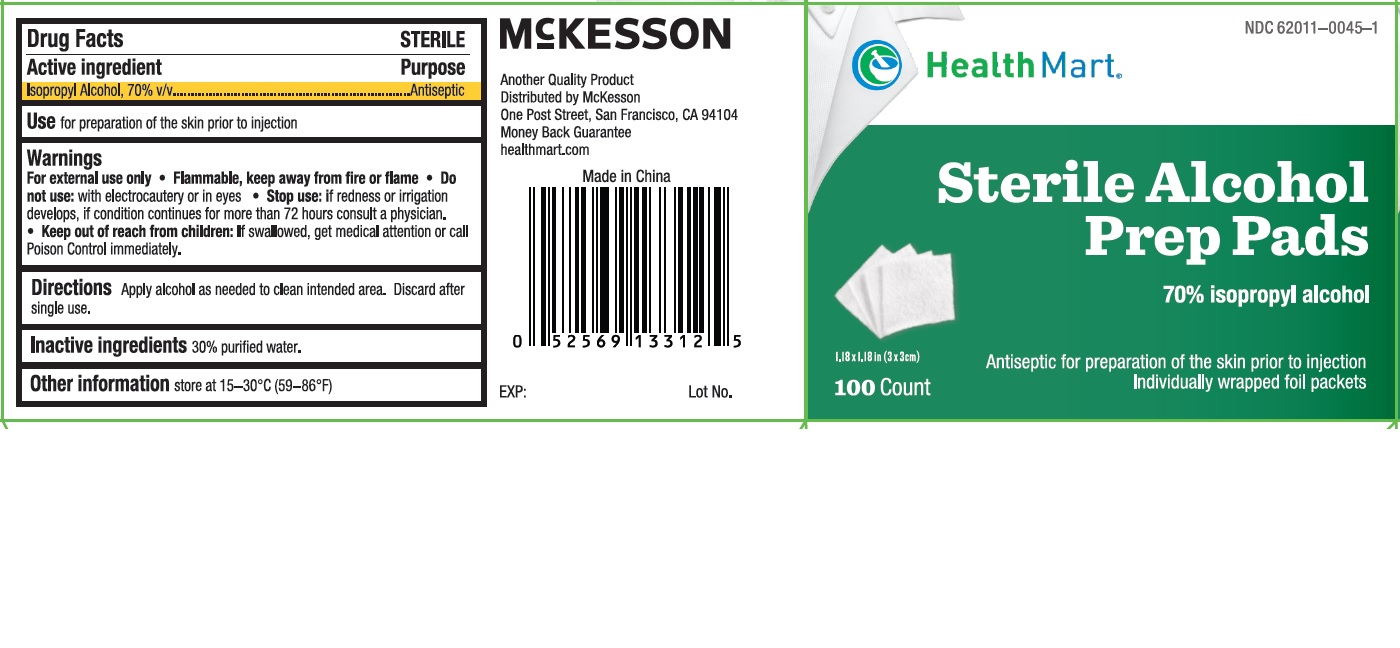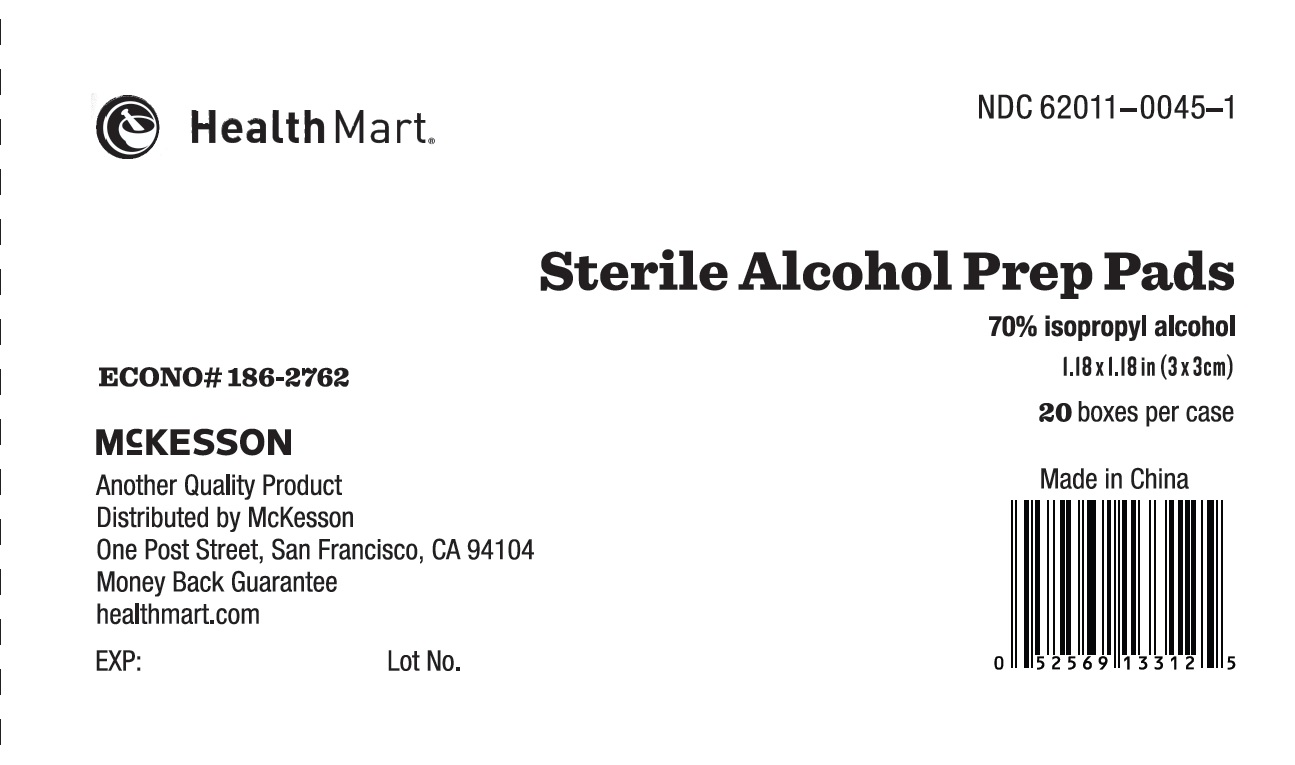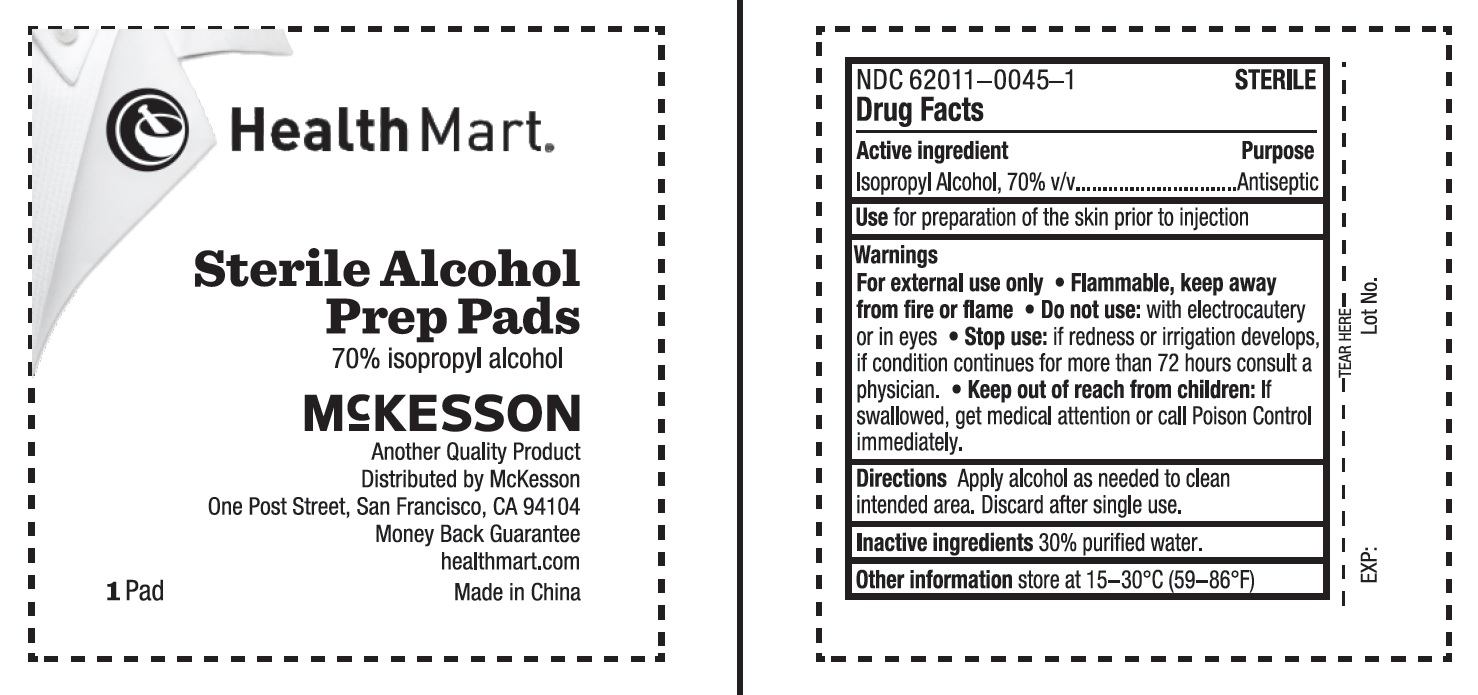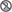 DRUG LABEL: Isopropyl Alcohol
NDC: 62011-0045 | Form: SWAB
Manufacturer: Strategic Sourcing Services LLC
Category: otc | Type: HUMAN OTC DRUG LABEL
Date: 20240307

ACTIVE INGREDIENTS: ISOPROPYL ALCOHOL 0.7 mL/1 1
INACTIVE INGREDIENTS: WATER

Alcohol prep pads

Drug Facts

STERILE

Active ingredient

Isopropyl Alcohol, 70% v/v

Purpose

Antiseptic

Use

for preparation of the skin prior to injection

Warnings

For external use only

- Flammable, keep away from fire or flame

- Do not use:with electrocautery or in eyes

- Stop use: if redness or irritation develops, if condition continues for more than 72 hours consult a physician.

KEEP OUT OF REACH OF CHILDREN

- Keep out of reach from Children:If swallowed, get medical attention or call Poison Control immediately.

Directions

Apply alcohol as needed to clean intended area. Discard after single use.

Inactive Ingredients

30% purified water.

Other Information

this product should be stored at room temperature: 59° - 86°F (15° - 30°C)

Principal Display Panel – Carton Label

NDC 62011-0045-1
HealthMart®
Sterile Alcohol Prep Pads

70% Isopropyl Alcohol
1.18 x 1.18 in (3 x 3 cm)

20 boxes per case
MFR# 186-2762

Another Quality Product
Distributed By McKesson
One Post Street, San Francisco, CA 94104
Money Back Guarantee
healthmart.com

Principal Display Panel – Box Label

NDC 62011-0045-1
HealthMart®
Sterile Alcohol Prep Pads

70% isopropyl alcohol
Antiseptic for preparation of the skin prior to injection
1.18 x 1.18 in (3 x 3 cm)
100 individually wrapped foil packets

MFR # 186-2762

Principal Display Panel – Pack Label

NDC 62011-0045-1
HealthMart ®
Sterile Alcohol Prep Pads

70% isopropyl alcohol
Antiseptic for preparation of the skin prior to injection
1.18 x 1.18 in (3 x 3 cm)
100 individually wrapped foil packets

MFR # 186-2762